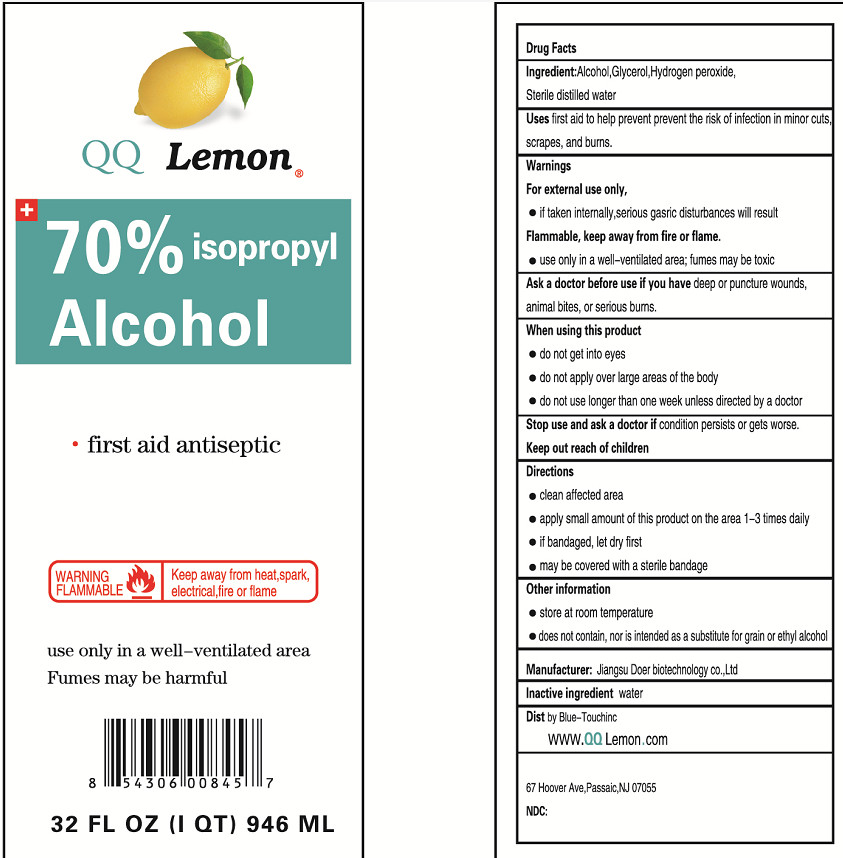 DRUG LABEL: DISINFECTANT ALCOHOL
NDC: 55449-004 | Form: LIQUID
Manufacturer: Jiangsu Doer biotechnology Co., Ltd
Category: otc | Type: HUMAN OTC DRUG LABEL
Date: 20201103

ACTIVE INGREDIENTS: ALCOHOL 662.2 mL/946 mL
INACTIVE INGREDIENTS: WATER; GLYCERIN; HYDROGEN PEROXIDE

55449-004 outcome

DOSAGE AND ADMINISTRATION

This is flammable product and required to be far away of any fire source.

INACTIVE INGREDIENT

WATER

HYDROGEN PEROXIDE

GLYCEROL

INDICATIONS AND USAGE

Please follow the instructions on the product label to use it correctly

ACTIVE INGREDIENT

alcohol

keep out of reach of children

PURPOSE

Disinfection
Sterilization
No Rinseing

WARNINGS

1.For external use only. If taken iteterally serious gastric disturbances will result.
2.Flammable: keep away from fire or flame,heat,spark, electrical.
3.When using this product: do not get into eyes;do not inhale; do not apply over large areas of the body.
4.Keep out of reach of chidren. If swallowed,get medical help or contact a Poison Control Center right away.